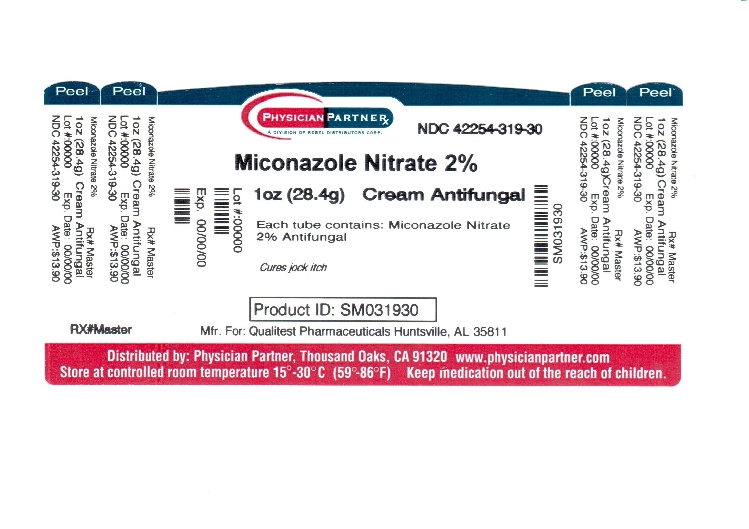 DRUG LABEL: Miconazole Nitrate
NDC: 42254-319 | Form: CREAM
Manufacturer: Rebel Distributors Corp
Category: otc | Type: HUMAN OTC DRUG LABEL
Date: 20121002

ACTIVE INGREDIENTS: MICONAZOLE NITRATE 20 mg/1 g
INACTIVE INGREDIENTS: BENZOIC ACID; BUTYLATED HYDROXYANISOLE; MINERAL OIL; PEG-5 OLEATE; PEGOXOL 7 STEARATE; WATER

Miconazole Nitrate 2% Cream

Active ingredient

Miconazole nitrate 2%

Purpose

Antifungal

Uses

- proven clinically effective in the treatment of most athlete's foot (tinea pedis), jock itch (tinea cruris) and ringworm (tinea corporis)
- relieves itching, scaling, cracking, burning and discomfort associated with those conditions

Do not use

on children under 2 years of age unless directed by a doctor

When using this product

avoid contact with the eyes

Stop use and ask a doctor if

- irritation occurs or if there is no improvement within 4 weeks (for athlete's foot and ringworm)
- irritation occurs or if there is no improvement within 2 weeks (for jock itch)

Keep out of reach of children.

If swallowed, get medical help or contact a Poison Control Center right away.

Directions

- clean the affected area and dry thoroughly
- apply a thin layer of the product over affected area twice daily (morning and night) or as directed by a doctor
- supervise children in the use of this product

For athlete's foot:

- use daily for 4 weeks. If condition persists longer, consult a doctor.
- pay special attention to the spaces between the toes
- wear well-fitting, ventilated shoes
- change shoes and socks at least once daily

For ringworm, use daily for 4 weeks. If condition persists longer, consult a doctor.

For jock itch, use daily for 2 weeks. If condition persists longer, consult a doctor.

This product is not effective on the scalp or nails.

Other information

- store at 15° - 30°C (59° - 86°F)
- lot number and expiration date: see crimp of tube or see box
- to open: unscrew cap, use pointed end on cap to puncture seal

You may report serious side effects to: 130 Vintage Drive, Huntsville, AL 35811.

Inactive ingredients

benzoic acid, butylated hydroxyanisole, mineral oil, peglicol 5 oleate, pegoxol 7 stearate, purified water

Made in the USA
for Qualitest Pharmaceuticals
Huntsville, AL 35811

Rev. 10/09 R2
8280719 7805

Repackaged by
Rebel Distributors Corp.
Thousand Oaks, CA 91320